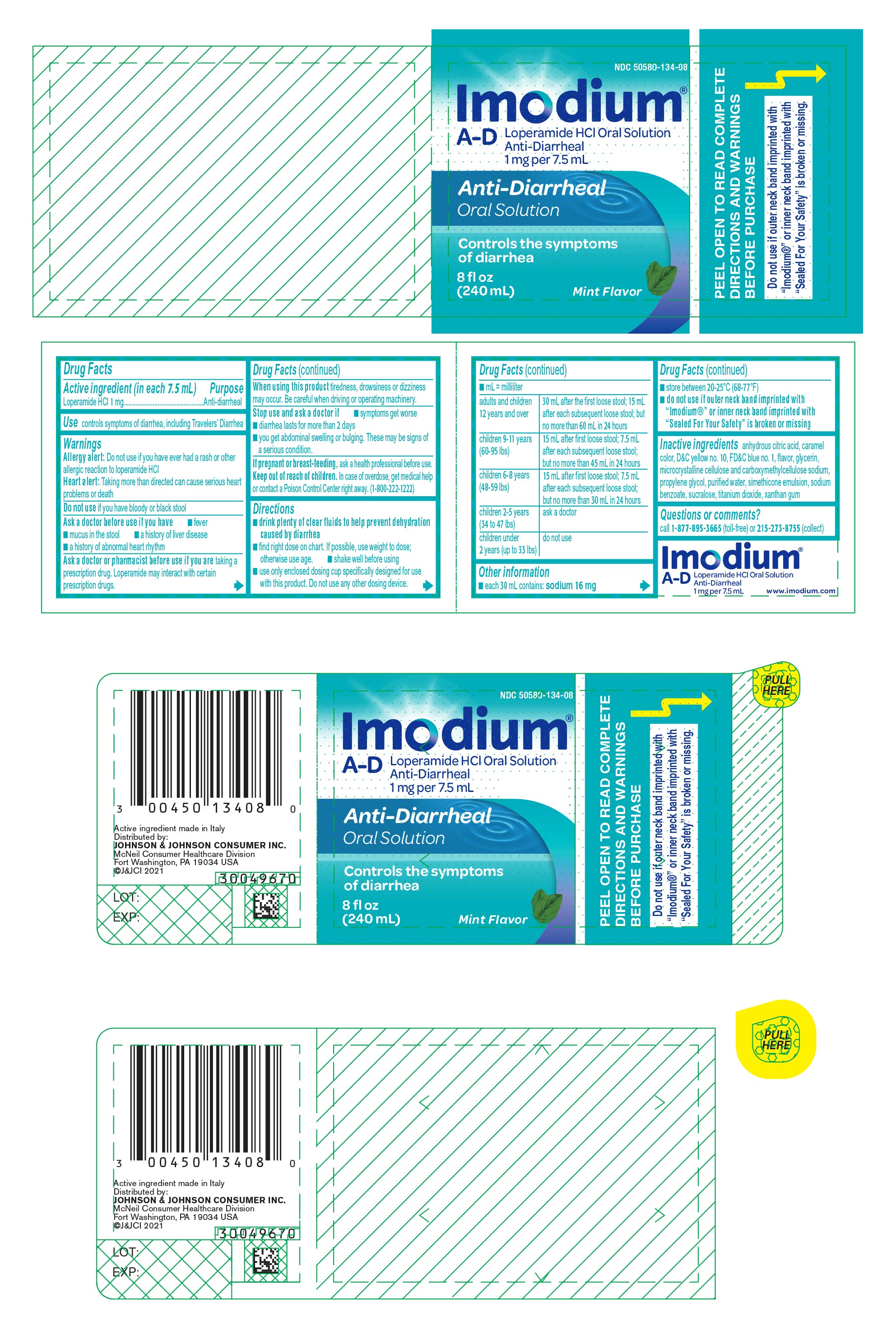 DRUG LABEL: Imodium
NDC: 50580-134 | Form: SOLUTION
Manufacturer: Kenvue Brands LLC
Category: otc | Type: HUMAN OTC DRUG LABEL
Date: 20250923

ACTIVE INGREDIENTS: LOPERAMIDE HYDROCHLORIDE 1 mg/7.5 mL
INACTIVE INGREDIENTS: CARBOXYMETHYLCELLULOSE SODIUM, UNSPECIFIED FORM; CARAMEL; D&C YELLOW NO. 10; FD&C BLUE NO. 1; GLYCERIN; MICROCRYSTALLINE CELLULOSE; PROPYLENE GLYCOL; SODIUM BENZOATE; SUCRALOSE; TITANIUM DIOXIDE; WATER; XANTHAN GUM; ANHYDROUS CITRIC ACID

IMODIUM
A-D

Drug Facts

Active ingredient (in each 7.5 mL)

Loperamide HCl 1 mg

Purpose

Anti-diarrheal

Use

controls symptoms of diarrhea, including Travelers' Diarrhea

Warnings

Allergy alert

Do not use if you have ever had a rash or other allergic reaction to loperamide HCl

Heart alert

Taking more than directed can cause serious heart problems or death

Do not use if you have bloody or black stool

Ask a doctor before use if you have

- fever
- mucus in the stool
- a history of liver disease
- a history of abnormal heart rhythm

Ask a doctor or pharmacist before use if you are taking a prescription drug. Loperamide may interact with certain prescription drugs.

When using this product tiredness, drowsiness or dizziness may occur. Be careful when driving or operating machinery.

Stop use and ask a doctor if

- symptoms get worse
- diarrhea lasts for more than 2 days
- you get abdominal swelling or bulging. These may be signs of a serious condition.

PREGNANCY OR BREAST FEEDING

If pregnant or breast-feeding, ask a health professional before use.

Keep out of reach of children. In case of overdose, get medical help or contact a Poison Control Center right away. (1-800-222-1222)

Directions

- drink plenty of clear fluids to help prevent dehydration caused by diarrhea
- find right dose on chart. If possible, use weight to dose; otherwise use age.
- shake well before using
- use only enclosed dosing cup specifically designed for use with this product. Do not use any other dosing device.
- mL = milliliter

adults and children 12 years and over | 30 mL after the first loose stool; 15 mL after each subsequent loose stool; but no more than 60 mL in 24 hours
children 9-11 years (60-95 lbs) | 15 mL after first loose stool; 7.5 mL after each subsequent loose stool; but no more than 45 mL in 24 hours
children 6-8 years (48-59 lbs) | 15 mL after first loose stool; 7.5 mL after each subsequent loose stool; but no more than 30 mL in 24 hours
children 2-5 years (34 to 47 lbs) | ask a doctor
children under 2 years (up to 33 lbs) | do not use

Other information

- each 30 mL contains: sodium 16 mg
- store between 20-25°C (68-77°F)
- do not use if outer neck band imprinted with "Imodium®" or inner neck band imprinted with "Sealed For Your Safety" is broken or missing

Inactive ingredients

anhydrous citric acid, caramel color, D&C yellow no. 10, FD&C blue no. 1, flavor, glycerin, microcrystalline cellulose and carboxymethylcellulose sodium, propylene glycol, purified water, simethicone emulsion, sodium benzoate, sucralose, titanium dioxide, xanthan gum

Questions or comments?

call 1-877-895-3665 (toll-free) or 215-273-8755 (collect)

PRINCIPAL DISPLAY PANEL

NDC 50580-134-08

Imodium®
A-D
Loperamide HCl Oral Solution

Anti-Diarrheal
1 mg per 7.5 mL

Anti-Diarrheal
Oral Solution

Controls the symptoms

of diarrhea

8 fl oz
(240 mL)

Mint Flavor